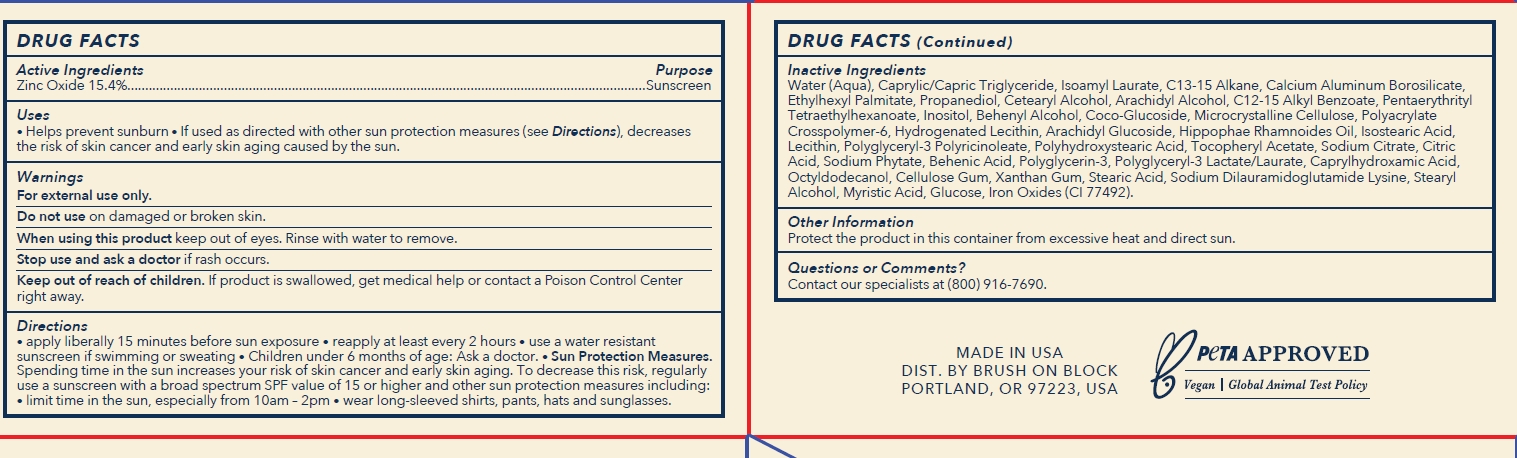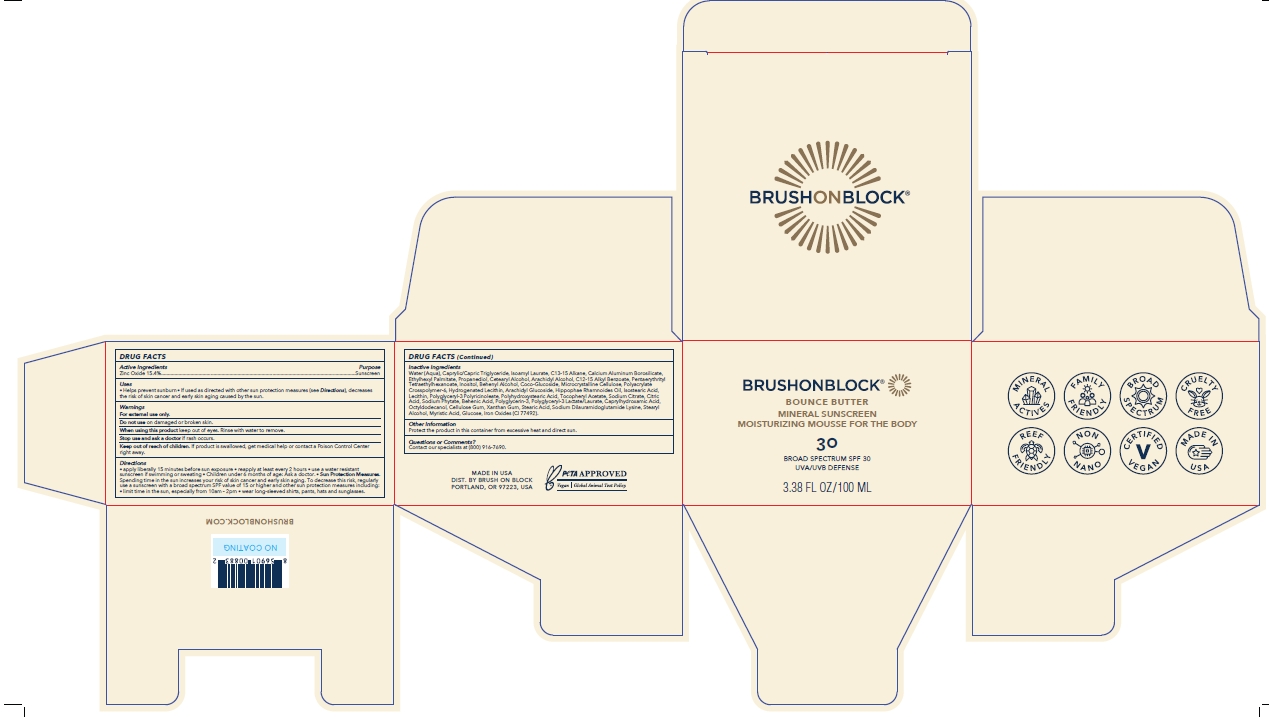 DRUG LABEL: Brush On Block Bounce Butter SPF 30 Moisturizing Mousse
NDC: 58274-014 | Form: LOTION
Manufacturer: SPF Ventures LLC
Category: otc | Type: HUMAN OTC DRUG LABEL
Date: 20240301

ACTIVE INGREDIENTS: ZINC OXIDE 15.4 g/100 mL
INACTIVE INGREDIENTS: STEARYL ALCOHOL; LECITHIN, SUNFLOWER; PHYTATE SODIUM; CALCIUM ALUMINUM BOROSILICATE; ETHYLHEXYL PALMITATE; ARACHIDYL ALCOHOL; BEHENIC ACID; DOCOSANOL; HYDROGENATED SOYBEAN LECITHIN; AMMONIUM ACRYLOYLDIMETHYLTAURATE, DIMETHYLACRYLAMIDE, LAURYL METHACRYLATE AND LAURETH-4 METHACRYLATE COPOLYMER, TRIMETHYLOLPROPANE TRIACRYLATE CROSSLINKED (45000 MPA.S); SODIUM CITRATE; SODIUM DILAURAMIDOGLUTAMIDE LYSINE; STEARIC ACID; MEDIUM-CHAIN TRIGLYCERIDES; ALKYL (C12-15) BENZOATE; CITRIC ACID MONOHYDRATE; OCTYLDODECANOL; PROPANEDIOL; C13-15 ALKANE; CETOSTEARYL ALCOHOL; PENTAERYTHRITYL TETRAETHYLHEXANOATE; ARACHIDYL GLUCOSIDE; CAPRYLHYDROXAMIC ACID; CARBOXYMETHYLCELLULOSE SODIUM, UNSPECIFIED FORM; COCO GLUCOSIDE; HIPPOPHAE RHAMNOIDES FRUIT OIL; INOSITOL; CELLULOSE, MICROCRYSTALLINE; TERT-BUTYL ALCOHOL; .ALPHA.-TOCOPHEROL ACETATE; FERRIC OXIDE YELLOW; WATER; ISOAMYL LAURATE; ANHYDROUS DEXTROSE; POLYGLYCERIN-3; POLYGLYCERYL-3 LAURATE; POLYGLYCERYL-3 PENTARICINOLEATE; ISOSTEARIC ACID; MYRISTIC ACID; XANTHAN GUM

Brush On Block Bounce Butter SPF 30 Moisturizing Mousse

Active Ingredients

Zinc Oxide 15.4%

Purpose

Sunscreen

Uses

- Helps prevent sunburn
- If used as directed with other sun protection measures (see Directions), decreases the risk of skin cancer and early skin aging caused by the sun.

Warnings

For external use only.

Do not use on damaged or broken skin

When using this product keep out of eyes. Rinse with water to remove.

Stop use and ask a doctor if rash occurs.

Keep out of reach of children

If product is swallowed, get medical help or contact a Poison Control Center right away.

Directions

- apply liberally 15 minutes before sun exposure.
- reapply at least every 2 hours
- use a water resistant sunscreen if swimming or sweating
- Children under 6 months of age: Ask a doctor.
- Sunprotection Measures. Spending time in the sun increases your risk of skin cancer and early skin aging. To decrease this risk, regularly use a sunscreen with a broad spectrum SPF value of 15 or higher and other sun protection measures including:
- limit time in the sun, especially from 10am-2pm
- wear long-sleeved shirts, pants, hats and sunglasses.

Inactive Ingredients

WATER (AQUA)

CAPRYLIC/CAPRIC TRIGLYCERIDE

ISOAMYL LAURATE

C13-15 ALKANE

CALCIUM SODIUM BOROSILICATE

ETHYLHEXYL PALMITATE

PROPANEDIOL

CETEARYL ALCOHOL

ARACHIDYL ALCOHOL

C12-15 ALKYL BENZOATE

PENTAERYTHRITYL TETRAETHYLHEXANOATE

ARACHIDYL GLUCOSIDE

BEHENIC ACID

BEHENYL ALCOHOL

CAPRYLHYDROXAMIC ACID

CELLULOSE GUM

CITRIC ACID

COCO-GLUCOSIDE

GLUCOSE

HIPPOPHAE RHAMNOIDES OIL

HYDROGENATED LECITHIN

INOSITOL

ISOSTEARIC ACID

LECITHIN

MICROCRYSTALLINE CELLULOSE

MYRISTIC ACID

OCTYLDODECANOL

POLYACRYLATE CROSSPOLYMER-6

POLYGLYCERIN-3

POLYGLYCERYL-3 LACTATE/LAURATE

POLYGLYCERYL-3 POLYRICINOLEATE

POLYHYDROXYSTEARIC ACID

SODIUM CITRATE

SODIUM DILAURAMIDOGLUTAMIDE LYSINE

SODIUM PHYTATE

STEARIC ACID

STEARYL ALCOHOL

T-BUTYL ALCOHOL

TOCOPHERYL ACETATE

XANTHAN GUM

IRON OXIDE (YELLOW) CI 77492

Other Information

Protect the product in this container from excessive heat and direct sun.